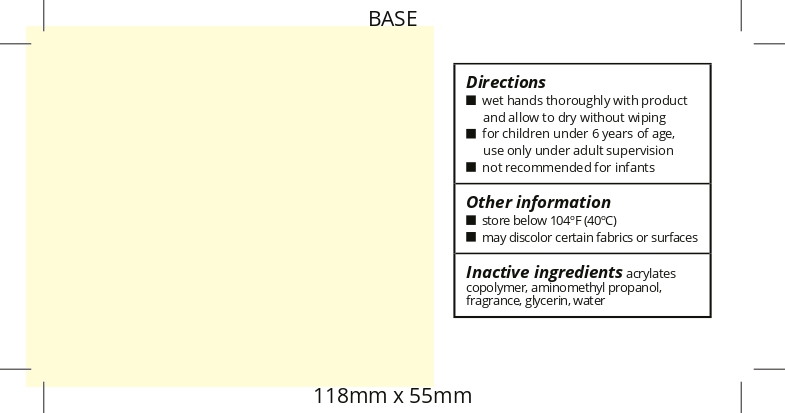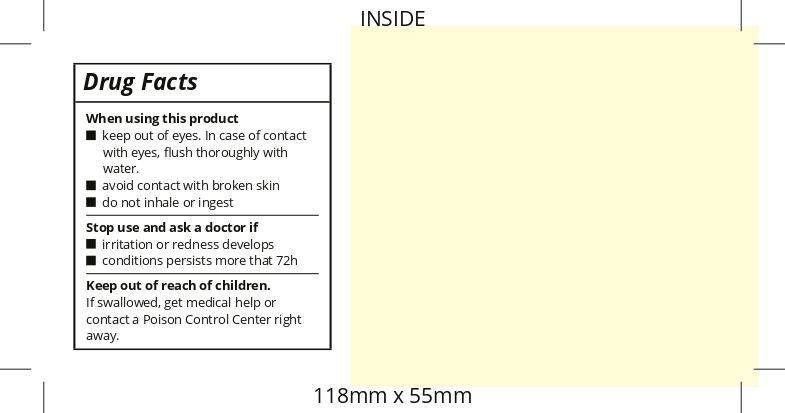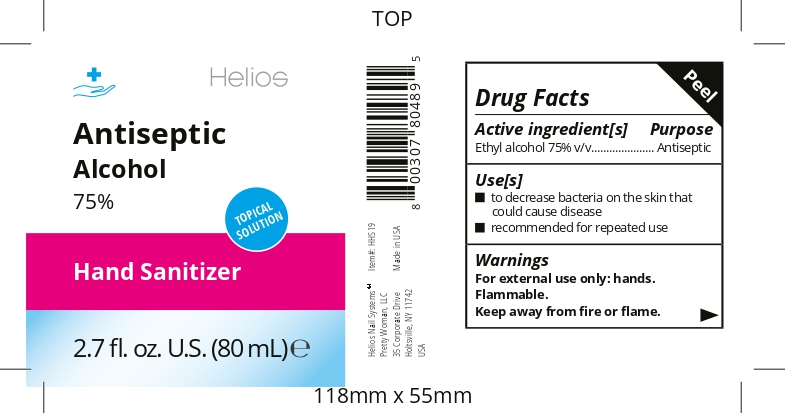 DRUG LABEL: HELIOS Hand Sanitizer
NDC: 74140-200 | Form: GEL
Manufacturer: Pretty Woman LLC
Category: otc | Type: HUMAN OTC DRUG LABEL
Date: 20200521

ACTIVE INGREDIENTS: ALCOHOL 75 mL/100 mL
INACTIVE INGREDIENTS: WATER; AMINOMETHYLPROPANOL; GLYCERIN; BUTYL ACRYLATE/METHYL METHACRYLATE/METHACRYLIC ACID COPOLYMER (18000 MW)

Helios Hand Sanitizer Gel 80 mL

Active Ingredient(s)

Ethyl alcohol 75% v/v. Purpose: Antiseptic

Purpose

Antiseptic, Hand Sanitizer

Use

- to decrease bacteria on the skin that could cause disease
- recommended for repeated use

Warnings

For external use only: hands. Flammable. Keep away from fire or flame.

When using this product

- keep out of eyes. In case of contact with eyes, flush thoroughly with water.
- avoid contact with broken skin
- do not inhale or ingest

Stop use and ask a doctor if

- irritation or redness develops
- conditions persists more that 72h

Keep out of reach of children. If swallowed, get medical help or contact a Poison Control Center right away.

Directions

- wet hands thoroughly with product and allow to dry without wiping
- for children under 6 years of age, use only under adult supervision
- not recommended for infants

Other information

- store below 104ºF (40ºC)
- may discolor certain fabrics or surfaces

Inactive ingredients

acrylates copolymer, aminomethyl propanol, fragrance, glycerin, water

Package Label - Principal Display Panel

80 mL NDC: 74140-200-01